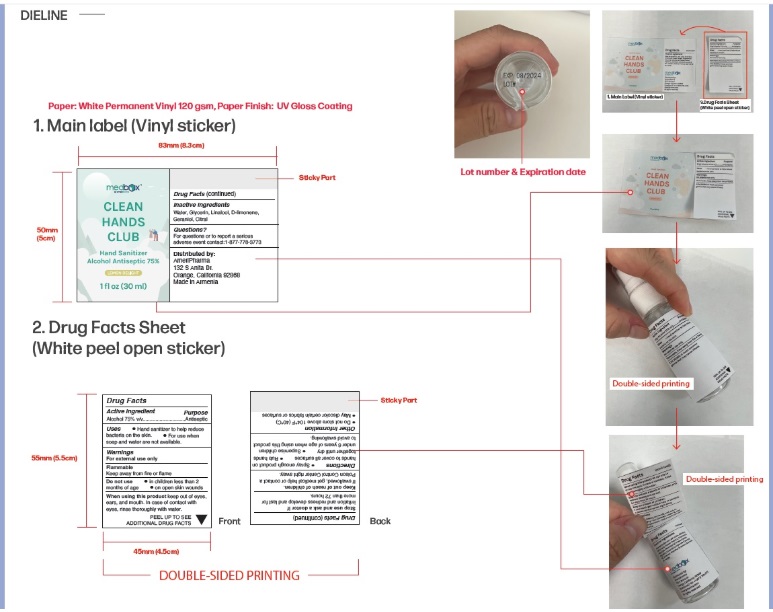 DRUG LABEL: MedBox Hand Sanitizer
NDC: 83638-001 | Form: LIQUID
Manufacturer: Harper’s Pharmacy, Inc.
Category: otc | Type: HUMAN OTC DRUG LABEL
Date: 20241220

ACTIVE INGREDIENTS: ALCOHOL 75 mL/100 mL
INACTIVE INGREDIENTS: WATER; GLYCERIN; LINALOOL, (+/-)-; LIMONENE, (+)-; GERANIOL; CITRAL

Active Ingredient

Alcohol 75% v/v

Purpose

Antiseptic

Uses

Hand sanitizer to help reduce bacteria on the skin. For use when soap and water are not available.

Warnings

For external use only.

Flammable
Keep away from fire or flame

Do not use

- in children less than 2 months of age
- on open skin wounds

When using this productkeep out of eyes,ears, and mouth. In case of contact with eyes, rinse thoroughly with water.

Stop use and ask a doctor if irritation and redness develop and last for more than 72 hours.

Keep out of reach of children.If swallowed, get medical help or contact aPoison Control Center right away.

Directions

- Spray enough product on hands to cover all surfaces
- Rub hands together until dry
- Supervise children under 6 years of age when using this product to avoid swallowing.

Other information

- Do not store above 104°F (40°C)
- May discolor certain fabrics or surfaces

Inactive ingredients

Water, Glycerin, Linalool, D-limonene, Geraniol, Citral